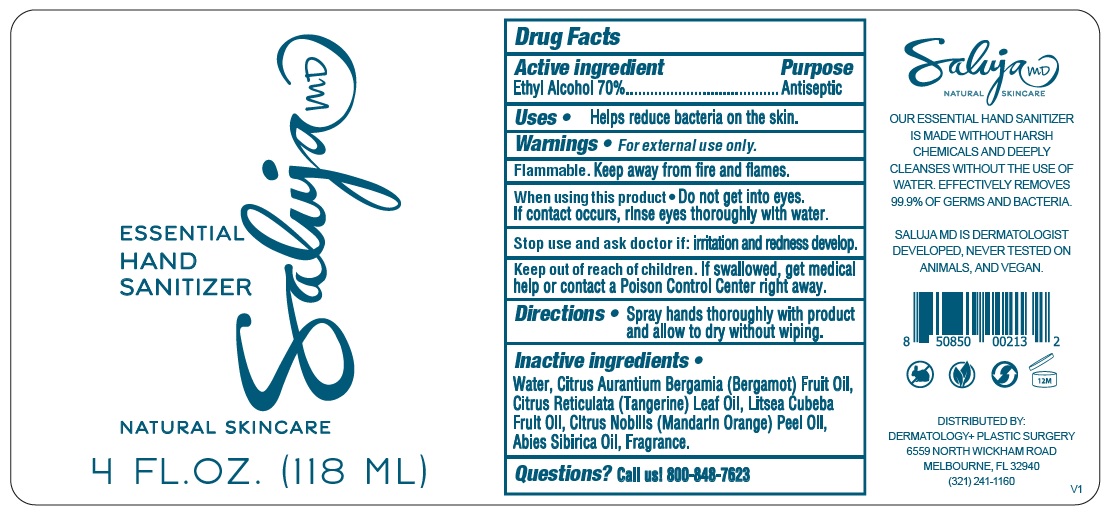 DRUG LABEL: Saluja MD Essential Hand Sanitizer
NDC: 81751-001 | Form: SPRAY
Manufacturer: Anita Saluja, Md, LLC
Category: otc | Type: HUMAN OTC DRUG LABEL
Date: 20241004

ACTIVE INGREDIENTS: ALCOHOL 70 mL/100 mL
INACTIVE INGREDIENTS: WATER; BERGAMOT OIL; CITRUS RETICULATA LEAF OIL; LITSEA OIL; MANDARIN OIL; ABIES SIBIRICA LEAF OIL

Saluja MD ESSENTIAL HAND SANITIZER

Active ingredient

Ethyl Alcohol 70%

Purpose

Antiseptic

Uses

• Helps reduce bacteria on the skin.

Warnings

• For external use only.

Flammable. Keep away from fire and flames.

When using this product • Do not get into eyes. If contact occurs, rinse eyes thoroughly with water.

Stop use and ask a doctor if: irritation and redness develop.

Keep out of reach of children. If swallowed, get medical help or contact a Poison Control Center right away.

Directions

• Spray hands thoroughly with product and allow to dry without wiping.

Inactive ingredients

• Water, Citrus Aurantium Bergamia (Bergamot) Fruit Oil, Citrus Reticulata (Tangerine) Leaf Oil, Litsea Cubeba Fruit Oil, Citrus Nobilis (Mandarin Orange) Peel Oil, Abies Sibirica Oil, Fragrance.

Questions?

Call us! 800-848-7623

NATURAL SKINCARE

OUR ESSENTIAL HAND SANITIZER IS MADE WITHOUT HARSH CHEMICALS AND DEEPLY CLEANSES WITHOUT THE USE OF WATER. EFFECTIVELY REMOVES 99.9% OF GERMS AND BACTERIA.

SALUJA MD IS DERMATOLOGIST DEVELOPED, NEVER TESTED ON ANIMALS, AND VEGAN.

DISTRIBUTED BY:

DERMATOLOGY+ PLASTIC SURGERY

6559 NORTH WICKHAM ROAD

MELBOURNE, FL 32940

(321) 241-1160